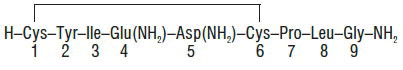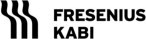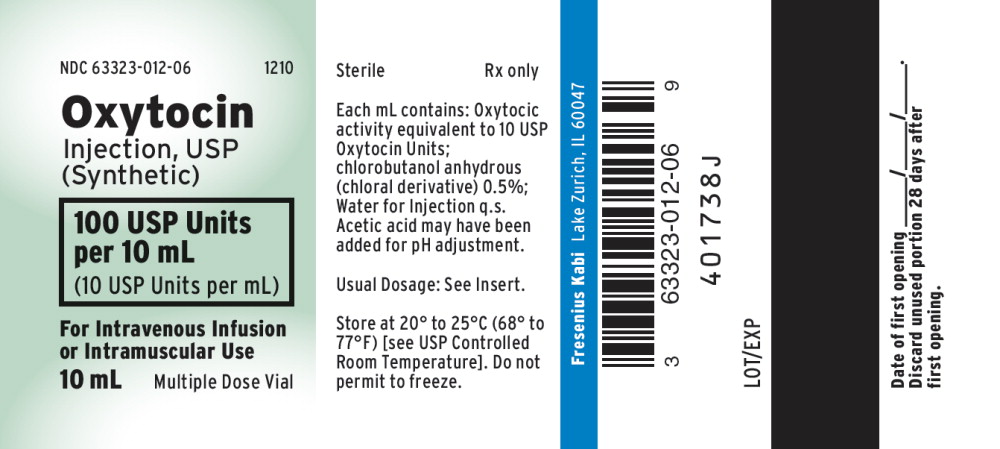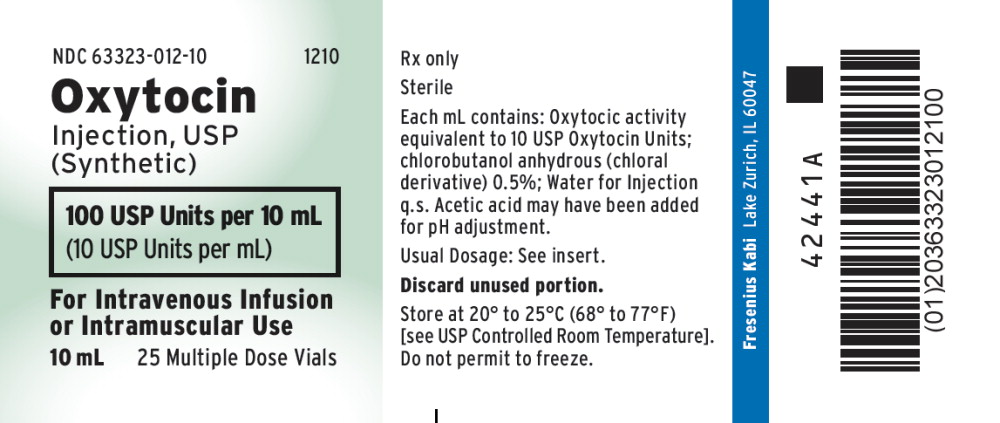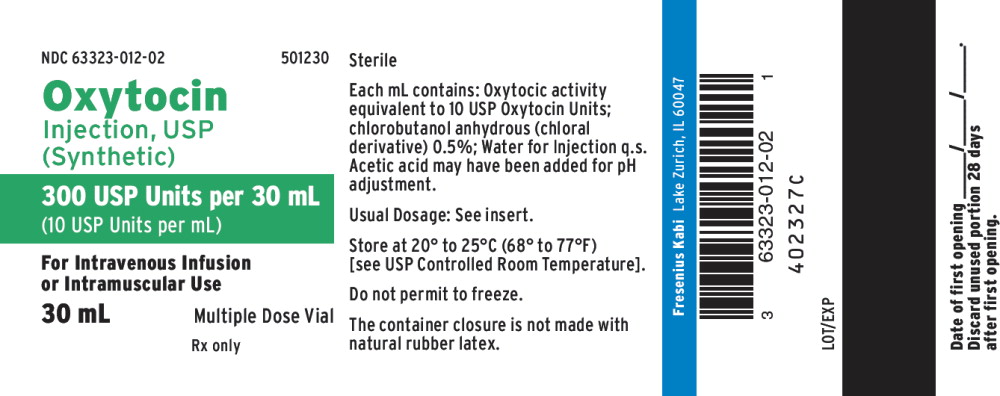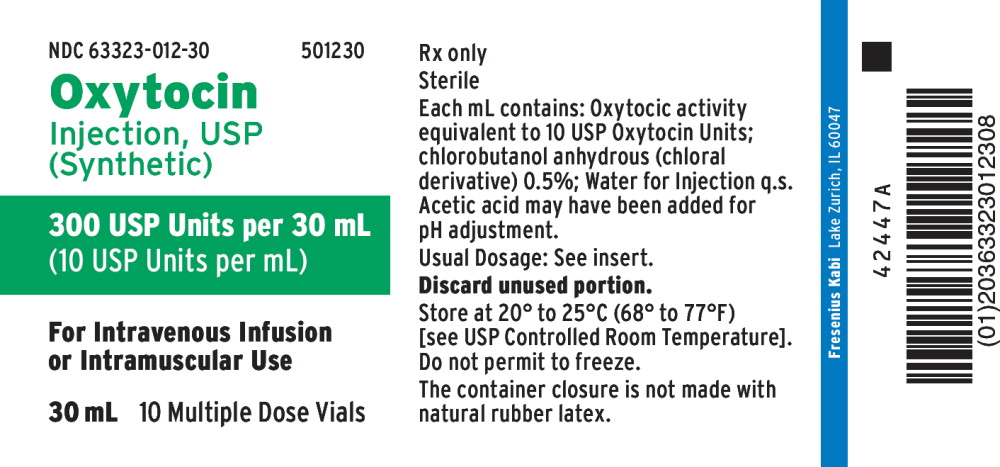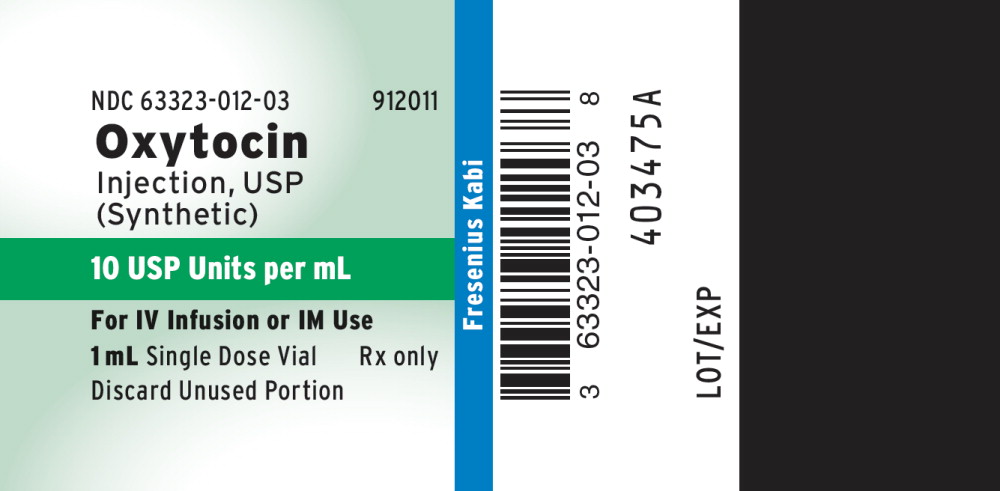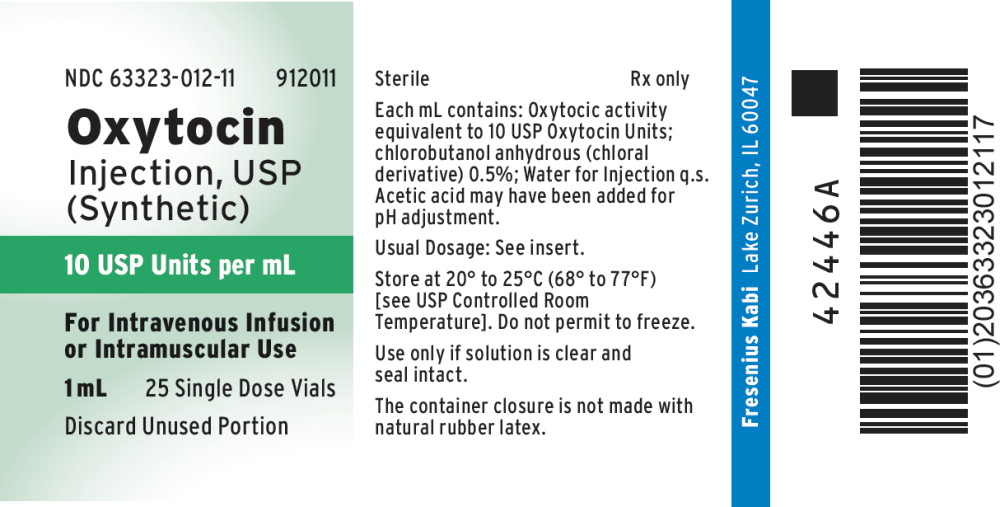 DRUG LABEL: Oxytocin
NDC: 63323-012 | Form: INJECTION, SOLUTION
Manufacturer: Fresenius Kabi USA, LLC
Category: prescription | Type: HUMAN PRESCRIPTION DRUG LABEL
Date: 20260112

ACTIVE INGREDIENTS: OXYTOCIN 10 [USP'U]/1 mL
INACTIVE INGREDIENTS: CHLOROBUTANOL; ACETIC ACID

Oxytocin Injection, USP

(SYNTHETIC)

FOR INTRAVENOUS INFUSION OR INTRAMUSCULAR USE

DESCRIPTION

Each mL of Oxytocin Injection, USP (synthetic), intended for intravenous infusion or intramuscular injection, possesses an oxytocic activity equivalent to 10 USP Oxytocin Units and contains chlorobutanol anhydrous (chloral derivative) 0.5%. This product may contain up to 12.5% decomposition products/impurities. Oxytocin injection (synthetic) is a sterile, clear, colorless solution of oxytocin in Water for Injection prepared by synthesis. Acetic acid may have been added for pH adjustment (pH 3.0-5.0). The structural formula is:

CLINICAL PHARMACOLOGY

Oxytocin injection (synthetic) acts on the smooth muscle of the uterus to stimulate contractions; response depends on the uterine threshold of excitability. It exerts a selective action on the smooth musculature of the uterus, particularly toward the end of pregnancy, during labor and immediately following delivery. Oxytocin stimulates rhythmic contractions of the uterus, increases the frequency of existing contractions and raises the tone of the uterine musculature. Synthetic oxytocin does not possess the cardiovascular effects, such as elevation of blood pressure, as exhibited by vasopressin found in posterior pituitary injection.

INDICATIONS AND USAGE

IMPORTANT NOTICE:

Oxytocin Injection, USP (synthetic) is indicated for the medical rather than the elective induction of labor. Available data and information are inadequate to define the benefits to risks considerations in the use of the drug product for elective induction. Elective induction of labor is defined as the initiation of labor for convenience in an individual with a term pregnancy who is free of medical indications.

Antepartum

Oxytocin injection (synthetic) is indicated for the initiation or improvement of uterine contractions, where this is desirable and considered suitable, in order to achieve early vaginal delivery for fetal or maternal reasons. It is indicated for (1) induction of labor in patients with a medical indication for the initiation of labor, such as Rh problems, maternal diabetes, pre-eclampsia at or near term, when delivery is in the best interest of mother and fetus or when membranes are prematurely ruptured and delivery is indicated; (2) stimulation or reinforcement of labor, as in selected cases of uterine inertia; (3) adjunctive therapy in the management of incomplete or inevitable abortion. In the first trimester, curettage is generally considered primary therapy. In second trimester abortion, oxytocin infusion will often be successful in emptying the uterus. Other means of therapy, however, may be required in such cases.

Postpartum

Oxytocin injection (synthetic) is indicated to produce uterine contractions during the third stage of labor and to control postpartum bleeding or hemorrhage.

CONTRAINDICATIONS

Oxytocin injection (synthetic) is contraindicated in any of the following conditions:

- Significant cephalopelvic disproportion;
- Unfavorable fetal positions or presentations which are undeliverable without conversion prior to delivery, i.e., transverse lies;
- In obstetrical emergencies where the benefit-to-risk ratio for either the fetus or the mother favors surgical intervention;
- In cases of fetal distress where delivery is not imminent;
- Prolonged use in uterine inertia or severe toxemia;
- Hypertonic uterine patterns;
- Patients with hypersensitivity to the drug;
- Induction or augmentation of labor in those cases where vaginal delivery is contraindicated, such as cord presentation or prolapse, total placenta previa, and vasa previa.

WARNINGS

Oxytocin injection (synthetic) when given for induction or stimulation of labor, must be administered only by the intravenous route and with adequate medical supervision in a hospital.

PRECAUTIONS

General

All patients receiving intravenous oxytocin must be under continuous observation by trained personnel with a thorough knowledge of the drug and qualified to identify complications. A physician qualified to manage any complications should be immediately available.

When properly administered, oxytocin should stimulate uterine contractions similar to those seen in normal labor. Overstimulation of the uterus by improper administration can be hazardous to both mother and fetus. Even with proper administration and adequate supervision, hypertonic contractions can occur in patients whose uteri are hypersensitive to oxytocin.

Except in unusual circumstances, oxytocin should not be administered in the following conditions: prematurity, borderline cephalopelvic disproportion, previous major surgery on the cervix or uterus including Caesarean section, overdistention of the uterus, grand multiparity or invasive cervical carcinoma. Because of the variability of the combinations of factors which may be present in the conditions above, the definition of ‘‘unusual circumstances’’ must be left to the judgement of the physician. The decision can only be made by carefully weighing the potential benefits which oxytocin can provide in a given case against rare but definite potential for the drug to produce hypertonicity or tetanic spasm.

Maternal deaths due to hypertensive episodes, subarachnoid hemorrhage, rupture of the uterus and fetal deaths due to various causes have been reported associated with the use of parenteral oxytocic drugs for induction of labor and for augmentation in the first and second stages of labor.

Oxytocin has been shown to have an intrinsic antidiuretic effect, acting to increase water reabsorption from the glomerular filtrate. Consideration should, therefore, be given to the possibility of water intoxication, particularly when oxytocin is administered continuously by infusion and the patient is receiving fluids by mouth.

Drug Interactions

Severe hypertension has been reported when oxytocin was given three to four hours following prophylactic administration of a vasoconstrictor in conjunction with caudal block anesthesia. Cyclopropane anesthesia may modify oxytocin’s cardiovascular effects, so as to produce unexpected results such as hypotension. Maternal sinus bradycardia with abnormal atrioventricular rhythms has also been noted when oxytocin was used concomitantly with cyclopropane anesthesia.

Carcinogenesis, Mutagenesis, Impairment of Fertility

There are no animal or human studies on the carcinogenicity and mutagenicity of this drug, nor is there any information on its effect on fertility.

Pregnancy Category C.

There are no known indications for use of oxytocin in the first and second trimester of pregnancy other than in relation to spontaneous or induced abortion. Based on the wide experience with this drug and its chemical structure and pharmacological properties, it would not be expected to present a risk of fetal abnormalities when used as indicated.

Nonteratogenic Effects—See ADVERSE REACTIONS in the fetus or infant.

Labor and Delivery—See INDICATIONS AND USAGE.

Nursing Mothers

It is not known whether this drug is excreted in human milk. Because many drugs are excreted in human milk, caution should be exercised when oxytocin is administered to a nursing woman.

ADVERSE REACTIONS

To report SUSPECTED ADVERSE REACTIONS, contact Fresenius Kabi USA, LLC at 1-800-551-7176 or FDA at 1-800-FDA-1088 or www.fda.gov/medwatch.

The following adverse reactions have been reported in the mother:

- Anaphylactic reaction
- Postpartum hemorrhage
- Cardiac arrhythmia
- Fatal afibrinogenemia
- Nausea
- Vomiting
- Premature ventricular contractions
- Pelvic hematoma

Excessive dosage or hypersensitivity to the drug may result in uterine hypertonicity, spasm, tetanic contraction or rupture of the uterus.

The possibility of increased blood loss and afibrinogenemia should be kept in mind when administering the drug.

Severe water intoxication with convulsions and coma has occurred, and is associated with a slow oxytocin infusion over a 24-hour period. Maternal death due to oxytocin-induced water intoxication has been reported.

The following adverse reactions have been reported in the fetus or infant:

Due to induced uterine mobility:

- Bradycardia
- Premature ventricular contractions and other arrhythmias
- Permanent CNS or brain damage
- Fetal death

Due to use of oxytocin in the mother:

- Neonatal retinal hemorrhage
- Low Apgar scores at five minutes
- Neonatal jaundice

OVERDOSAGE

Overdosage with oxytocin injection (synthetic) depends essentially on uterine hyperactivity whether or not due to hypersensitivity to this agent. Hyperstimulation with strong (hypertonic) or prolonged (tetanic) contractions, or a resting tone of 15 to 20 mm H2O or more between contractions can lead to tumultuous labor, uterine rupture, cervical and vaginal lacerations, postpartum hemorrhage, uteroplacental hypoperfusion and variable deceleration of fetal heart, fetal hypoxia, hypercapnia or death. Water intoxication with convulsions, which is caused by the inherent antidiuretic effect of oxytocin, is a serious complication that may occur if large doses (40 to 50 milliunits/minute) are infused for long periods. Management consists of immediate discontinuation of oxytocin, and symptomatic and supportive therapy.

DOSAGE AND ADMINISTRATION

Dosage of oxytocin is determined by uterine response. The following dosage information is based upon the various regimens and indications in general use.

Induction or Stimulation of Labor

Intravenous infusion (drip method) is the only acceptable method of administration for the induction or stimulation of labor.

Accurate control of the rate of infusion flow is essential. An infusion pump or other such device and frequent monitoring of strength of contractions and fetal heart rate are necessary for the safe administration of oxytocin for the induction or stimulation of labor. If uterine contractions become too powerful, the infusion can be abruptly stopped, and oxytocic stimulation of the uterine musculature will soon wane.

An intravenous infusion of a non-oxytocin containing solution should be started. Physiologic electrolyte solutions should be used except under unusual circumstances.

To prepare the usual solution for intravenous infusion–one mL (10 units) is combined aseptically with 1,000 mL of a non-hydrating diluent.

The combined solution, rotated in the infusion bottle to insure thorough mixing, contains 10 mU/mL. Add the container with dilute oxytocic solution to the system through the use of a constant infusion pump or other such device to control accurately the rate of infusion.

The initial dose should be no more than 1 to 2 mU/min. The dose may be gradually increased in increments of no more than 1 to 2 mU/min., until a contraction pattern has been established which is similar to normal labor.

The fetal heart rate, resting uterine tone, and the frequency, duration, and force of contractions should be monitored.

The oxytocin infusion should be discontinued immediately in the event of uterine hyperactivity or fetal distress. Oxygen should be administered to the mother. The mother and fetus must be evaluated by the responsible physician.

Control of Postpartum Uterine Bleeding

Intravenous Infusion (Drip Method)—To control postpartum bleeding, 10 to 40 units of oxytocin may be added to 1,000 mL of a nonhydrating diluent and run at a rate necessary to control uterine atony.

Intramuscular Administration—1 mL (10 units) of oxytocin can be given after delivery of the placenta.

Treatment of Incomplete or Inevitable Abortion

Intravenous infusion with physiologic saline solution, 500 mL, or 5% dextrose in physiologic saline solution to which 10 units of oxytocin have been added should be infused at a rate of 20 to 40 drops/minute.

Parenteral drug products should be inspected visually for particulate matter and discoloration prior to administration, whenever solution and container permit.

HOW SUPPLIED

Oxytocin Injection, USP (synthetic) is supplied as follows:

Product Code | Unit of Sale | Strength | Each
RF912011† | NDC 65219-021-01 Unit of 25 | 10 USP Units per mL | NDC 65219-021-00 1 mL fill in a 2 mL Single-dose Vial This product contains an RFID.
912011† | NDC 63323-012-11 Unit of 25 | 10 USP Units per mL | NDC 63323-012-03 1 mL fill in a 2 mL Single-dose Vial
1210 | NDC 63323-012-10 Unit of 25 | 100 USP Units per 10 mL (10 USP Units per mL) | NDC 63323-012-06 10 mL fill in a 10 mL Multiple-dose Vial
501230† | NDC 63323-012-30 Unit of 10 | 300 USP Units per 30 mL (10 USP Units per mL) | NDC 63323-012-02 30 mL fill in a 30 mL Multiple-dose Vial
† The container closure is not made with natural rubber latex

Discard unused portion.

Use only if solution is clear and seal intact.

Store at 20° to 25°C (68° to 77°F) [see USP Controlled Room Temperature].

Do not permit to freeze.

Manufactured by:

Lake Zurich, IL 60047
www.fresenius-kabi.com/us

45789H

Revised: July 2023

PACKAGE LABEL

PACKAGE LABEL – PRINCIPAL DISPLAY – Oxytocin 10 mL Multiple Dose Vial Label

NDC 63323-012-06 1210

Oxytocin Injection, USP

(Synthetic)

100 USP Units per 10 mL

(10 USP Units per mL)

For Intravenous Infusion

Or Intramuscular Use

10 mL Multiple Dose Vial Rx only

PACKAGE LABEL

PACKAGE LABEL – PRINCIPAL DISPLAY – Oxytocin 10 mL Multiple Dose Vial Tray Label

NDC 63323-012-10 1210

Oxytocin Injection, USP

(Synthetic)

100 USP Units per 10 mL

(10 USP Units per mL)

For Intravenous Infusion

Or Intramuscular Use

10 mL 25 Multiple Dose Vials Rx only

PACKAGE LABEL

PACKAGE LABEL – PRINCIPAL DISPLAY – Oxytocin 30 mL Multiple Dose Vial Label

NDC 63323-012-02 501230

Oxytocin Injection, USP

(Synthetic)

300 USP Units per 30 mL

(10 USP Units per mL)

For Intravenous Infusion

Or Intramuscular Use

30 mL Multiple Dose Vial Rx only

PACKAGE LABEL

PACKAGE LABEL – PRINCIPAL DISPLAY – Oxytocin 1 mL Single Dose Vial Label

NDC 63323-012-30 501230

Oxytocin Injection, USP

(Synthetic)

300 USP Units per 30 mL

(10 USP Units per mL)

For Intravenous Infusion

Or Intramuscular Use

30 mL 10 Multiple Dose Vials Rx only

PACKAGE LABEL

PACKAGE LABEL – PRINCIPAL DISPLAY – Oxytocin 30 mL Multiple Dose Vial Label

NDC 63323-012-03 912011

Oxytocin Injection, USP

(Synthetic)

10 USP Units per mL

For IV Infusion or IM Use

1 mL Single Dose Vial

Discard Unused Portion Rx only

PACKAGE LABEL

PACKAGE LABEL – PRINCIPAL DISPLAY – Oxytocin 30 mL Multiple Dose Vial Tray Label

NDC 63323-012-11 912011

Oxytocin Injection, USP

(Synthetic)

10 USP Units per mL

For Intravenous Infusion

Or Intramuscular Use

1 mL 25 Single Dose Vial

Discard Unused Portion Rx only